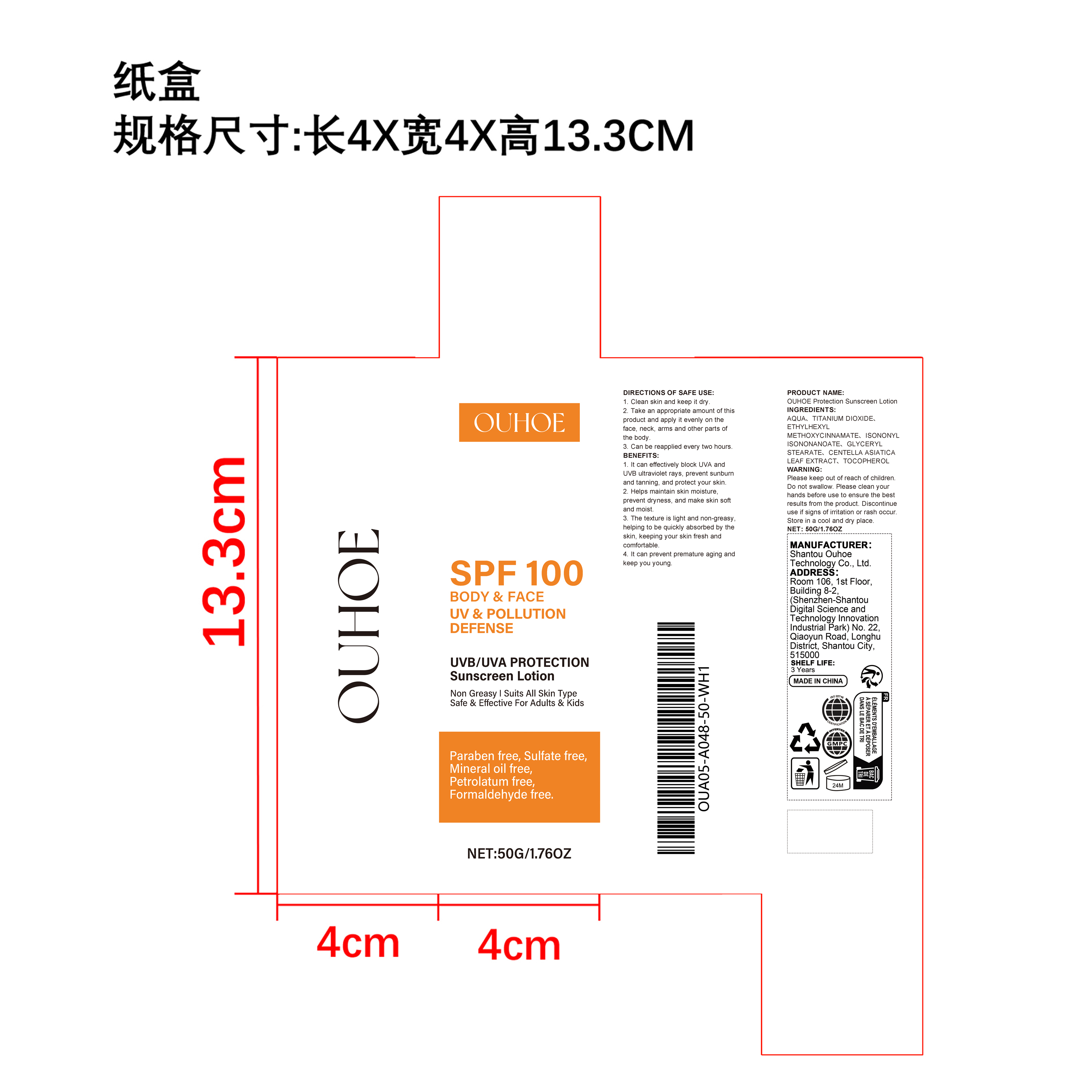 DRUG LABEL: OUHOE Protection Sunscreen
NDC: 85163-008 | Form: LIQUID
Manufacturer: Shantou Ouhoe Technology Co., Ltd.
Category: otc | Type: HUMAN OTC DRUG LABEL
Date: 20251127

ACTIVE INGREDIENTS: CENTELLA ASIATICA 0.15 mg/50 mg
INACTIVE INGREDIENTS: ETHYLHEXYL METHOXYCINNAMATE 2.5 mg/50 mg; AQUA 40.59 mg/50 mg; GLYCERYL STEARATE 0.75 mg/50 mg; TOCOPHEROL 0.01 mg/50 mg; TITANIUM DIOXIDE 4 mg/50 mg; ISONONYL ISONONANOATE 2 mg/50 mg

ACTIVE INGREDIENT

CENTELLA ASIATICA LEAF EXTRACT

PURPOSE

1. It can effectively block UVA and UVB ultraviolet rays, prevent sunburn and tanning, and protect your skin.

2. Helps maintain skin moisture, prevent dryness, and make skin soft and moist.

3. The texture is light and non-greasy, helping to be quickly absorbed by the skin, keeping your skin fresh and comfortable.

4. It can prevent premature aging and keep you young.

WHEN USING

1. Clean skin and keep it dry

2. Take an appropriate amount of this product and apply it evenly on the face, neck, arms and other parts of the body.

3. Can be reapplied every two hours

WARNINGS

Please keep out of reach of children. Do not swallow.Please clean your hands before use to ensure the best results from the product. Discontinue use if signs of irritation or rash occur. Store in a cool and dry place.

DO NOT USE

Discontinue use if signs of irritation or rash occur.

STOP USE

Discontinue use if signs of irritation or rash occur.

KEEP OUT OF REACH OF CHILDREN

Please keep out of reach of children. Do not swallow.

STORAGE AND HANDLING

Store in a cool and dry place.

INACTIVE INGREDIENT

AQUA,、TITANIUM DIOXIDE、ETHYLHEXYL METHOXYCINNAMATE、 ISONONYL ISONONANOATE、 GLYCERYL STEARATE、TOCOPHEROL

INDICATIONS AND USAGE

1. Clean skin and keep it dry

2. Take an appropriate amount of this product and apply it evenly on the face, neck, arms and other parts of the body.

3. Can be reapplied every two hours

DOSAGE AND ADMINISTRATION

1. Clean skin and keep it dry

2. Take an appropriate amount of this product and apply it evenly on the face, neck, arms and other parts of the body.

3. Can be reapplied every two hours